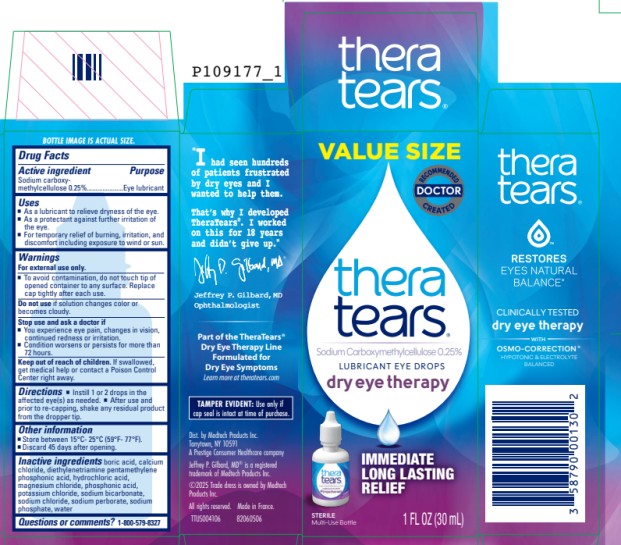 DRUG LABEL: TheraTears Lubricant
NDC: 58790-001 | Form: SOLUTION/ DROPS
Manufacturer: MEDTECH PRODUCTS INC
Category: otc | Type: HUMAN OTC DRUG LABEL
Date: 20251023

ACTIVE INGREDIENTS: carboxymethylcellulose sodium 2.5 mg/1 mL
INACTIVE INGREDIENTS: boric acid; sodium perborate; calcium chloride; diethylenetriamine pentamethylene phosphonic acid; magnesium chloride; potassium chloride; water; sodium bicarbonate; sodium chloride; sodium phosphate

TheraTears MD 58790-001

Drug Facts

Active ingredient

Sodium carboxy-
methylcellulose 0.25%

Purpose

Eye lubricant

Uses

- As a lubricant to relieve dryness of the eye.
- As a protectant against further irritation of the eye.
- For temporary relief of burning, irritation, and discomfort including exposure to wind or sun.

Warnings

For external use only

- To avoid contamination do not touch tip of opened container to any surface. Replace cap after using.

Do not use

- If solution changes color or becomes cloudy.

Stop use and ask a doctor if

- You experience eye pain, changes in vision, continued redness or irritation.
- Condition worsens or persists for more than 72 hours.

Keep out of reach of children.

If swallowed, get medical help or contact a Poison Control Center immediately.

Directions

- Instill 1 or 2 drops in the affected eye(s) as needed.
- After use and prior to re-capping, shake any residual product from the dropper tip.

Other information

- Store between 15-25C (59-77F)
- Discard 45 days after opening.

Inactive ingredients

boric acid, calcium chloride, diethylenetriamine pentamethylene phosphonic acid, hydrochloric acid, magnesium chloride, phosphonic acid, potassium chloride, sodium bicarbonate, sodium chloride, sodium perborate, sodium phosphate, water

Questions or comments?

1-800-579-8327

Principal Display Panel Text for Carton Label:

thera

tears®

LUBRICANT

EYE DROPS

1 FL OZ (30 mL)